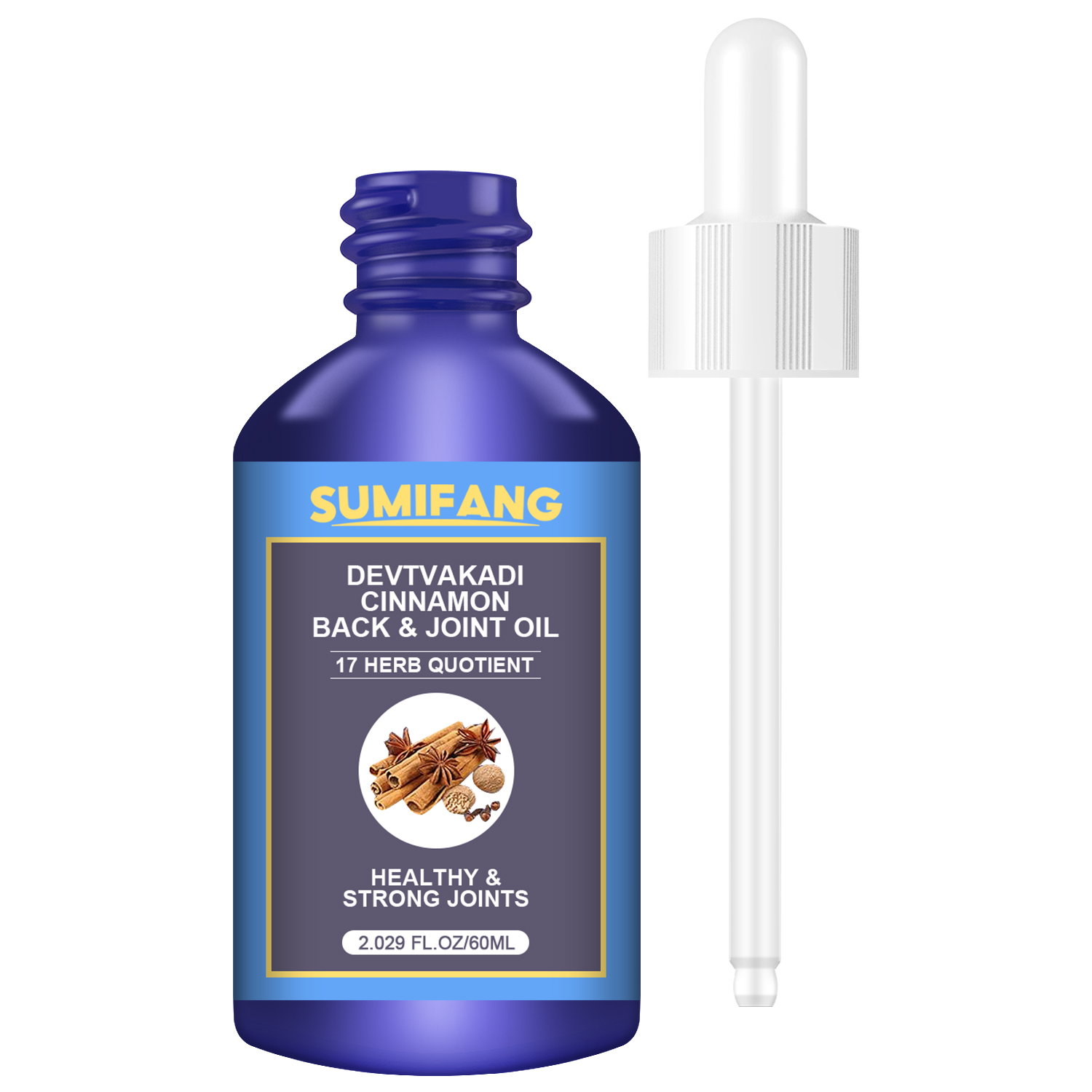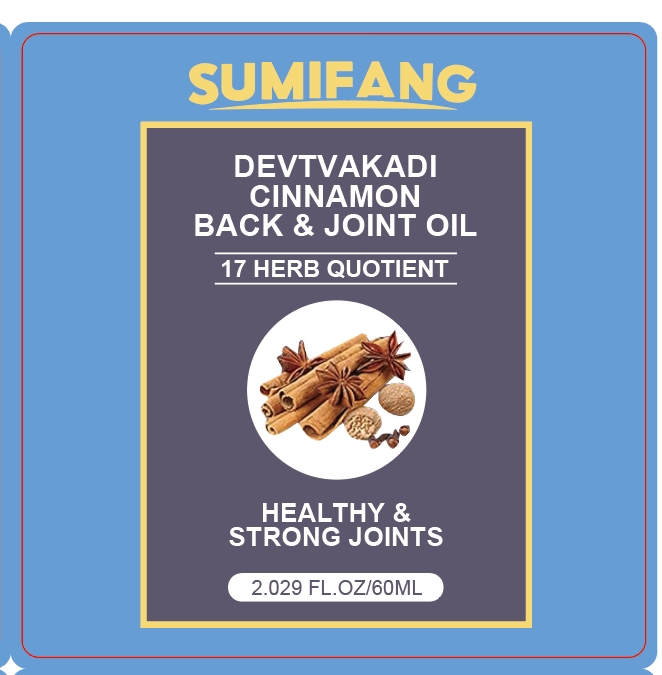 DRUG LABEL: BACK JOINTOIL
NDC: 84025-100 | Form: LIQUID
Manufacturer: Guangzhou Yanxi Biotechnology Co., Ltd
Category: otc | Type: HUMAN OTC DRUG LABEL
Date: 20240801

ACTIVE INGREDIENTS: ALLANTOIN 3 mg/60 mL; 1,2-BUTANEDIOL 5 mg/60 mL
INACTIVE INGREDIENTS: WATER

DOSAGE AND ADMINISTRATION

Essential oils for daily skin care

WARNINGS

keep out of children

INACTIVE INGREDIENT

Aqua

INDICATIONS AND USAGE

For Daily Skin Care

keep out of children

PURPOSE

Nourishes and smoothes the skin